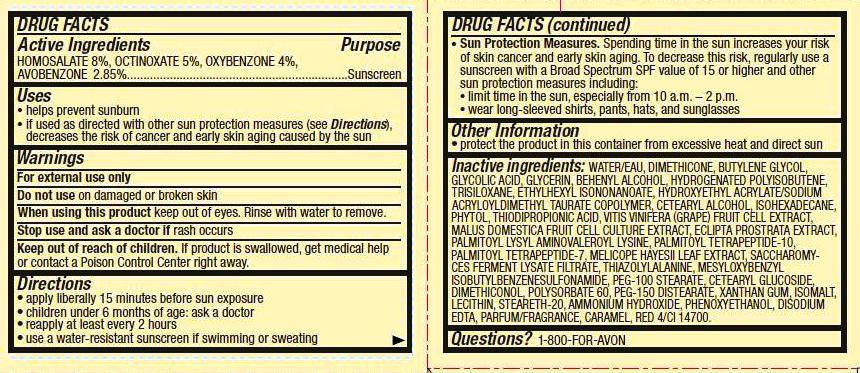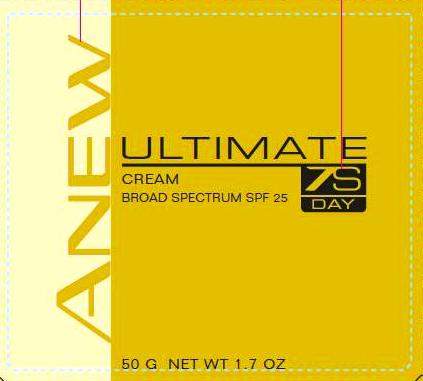 DRUG LABEL: Anew 
NDC: 10096-0266 | Form: CREAM
Manufacturer: Avon Products, Inc.
Category: otc | Type: HUMAN OTC DRUG LABEL
Date: 20111220

ACTIVE INGREDIENTS: HOMOSALATE	 4 g/50 g; OCTINOXATE	 2.5 g/50 g; OXYBENZONE	 2 g/50 g; AVOBENZONE 1.425 g/50 g

Drug Facts

Active ingredients
HOMOSALATE 8%, OCTINOXATE 5%, OXYBENZONE 4%,
AVOBENZONE 2.85%...................................................................

Purpose
....................................................Sunscreen

Uses
• helps prevent sunburn

• if used as directed with other sun protection measures (see Directions), decreases the risk of cancer and early skin aging caused by the sun

Warnings
For external use only

Do not use on damaged or broken skin

When using this product keep out of eyes. Rinse with water to remove.

Stop use and ask a doctor if rash occurs

Keep out of reach of children. If swallowed, get medical help or contact a Poison Control Center right away.

Directions
• apply liberally 15 minutes before sun exposure
• children under 6 months of age: ask a doctor
• reapply at least every 2 hours
• use a water resistant sunscreen if swimming or sweating

• Sun Protection Measures. Spending time in the sun increases your risk of skin cancer and early skin aging. To decrease this risk, regularly use a sunscreen with a Broad Spectrum SPF value of 15 or higher and other sun protection measures including:
• limit time in the sun, especially from 10 a.m. – 2 p.m.
• wear long-sleeved shirts, pants, hats, and sunglasses

Other information
• protect the product in this container from excessive heat and direct sun

INACTIVE INGREDIENT

Inactive ingredients: WATER/EAU, DIMETHICONE, BUTYLENE GLYCOL, GLYCOLIC ACID, GLYCERIN, BEHENYL ALCOHOL, HYDROGENATED POLYISOBUTENE, TRISILOXANE, ETHYLHEXYL ISONONANOATE, HYDROXYETHYL ACRYLATE/SODIUM ACRYLOYLDIMETHYL TAURATE COPOLYMER, CETEARYL ALCOHOL, ISOHEXADECANE, PHYTOL, THIODIPROPIONIC ACID, VITIS VINIFERA (GRAPE) FRUIT CELL EXTRACT, MALUS DOMESTICA FRUIT CELL CULTURE EXTRACT, ECLIPTA PROSTRATA EXTRACT, PALMITOYL LYSYL AMINOVALEROYL LYSINE, PALMITOYL TETRAPEPTIDE-10, PALMITOYL TETRAPEPTIDE-7, MELICOPE HAYESII LEAF EXTRACT, SACCHAROMYCES FERMENT LYSATE FILTRATE, THIAZOLYLALANINE, MESYLOXYBENZYL ISOBUTYLBENZENESULFONAMIDE, PEG-100 STEARATE, CETEARYL GLUCOSIDE, DIMETHICONOL, POLYSORBATE 60, PEG-150 DISTEARATE, XANTHAN GUM, ISOMALT, LECITHIN, STEARETH-20, AMMONIUM HYDROXIDE, PHENOXYETHANOL, DISODIUM EDTA, PARFUM/FRAGRANCE, CARAMEL, RED 4/CI 14700.

Questions? 1-800-FOR-AVON